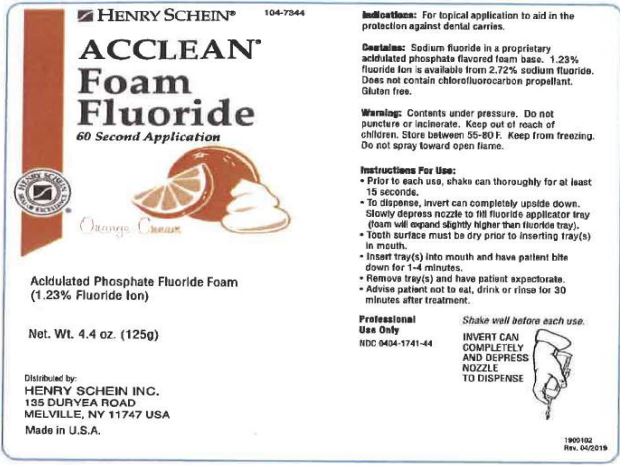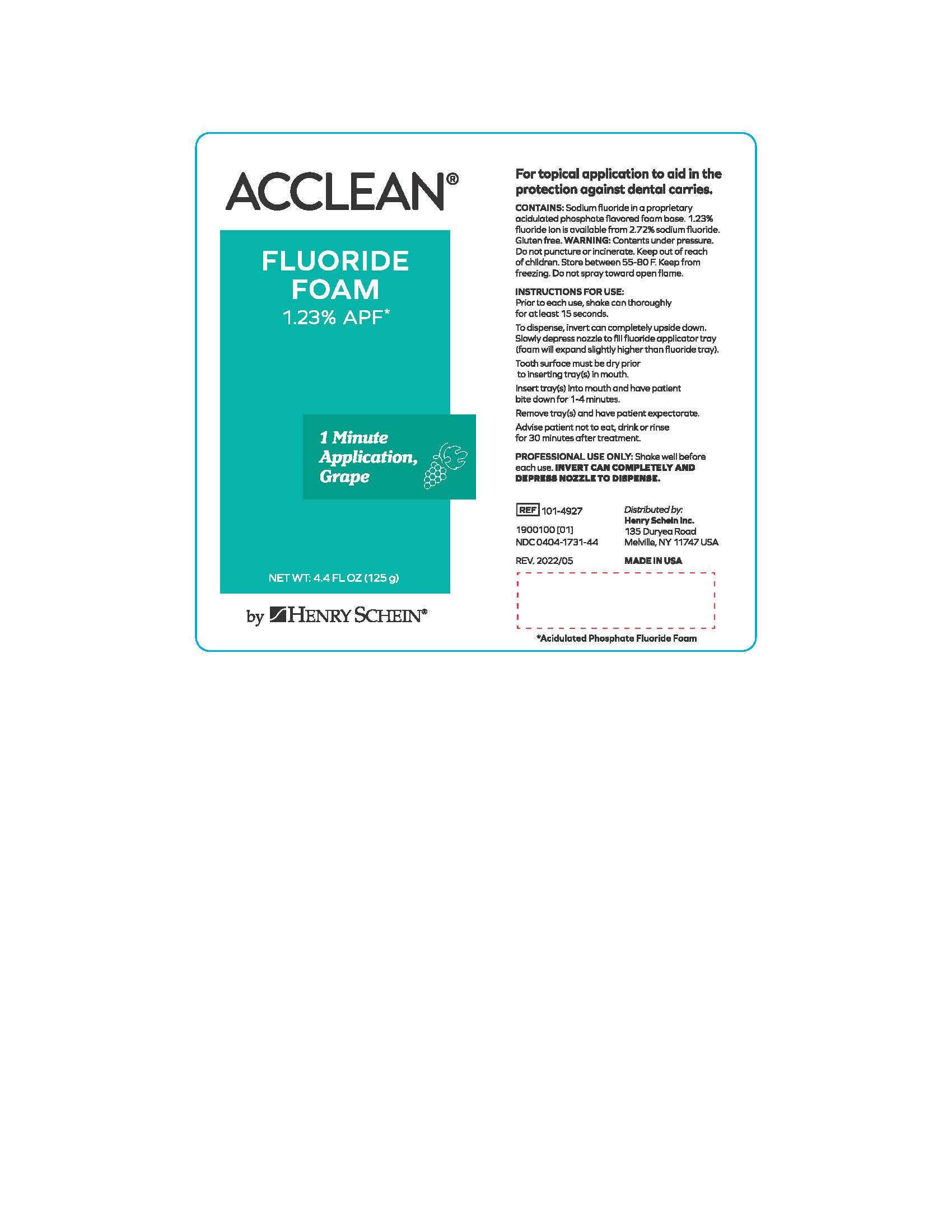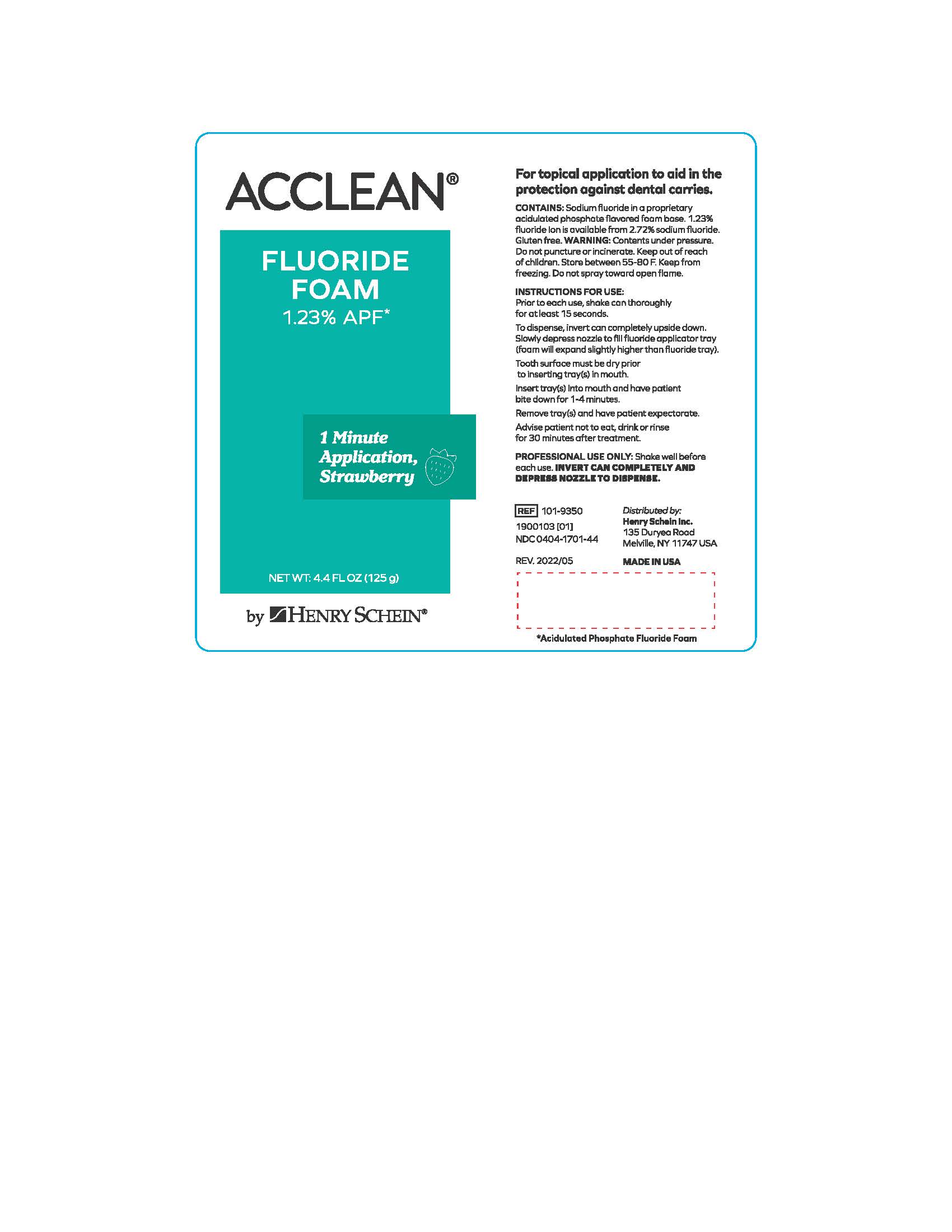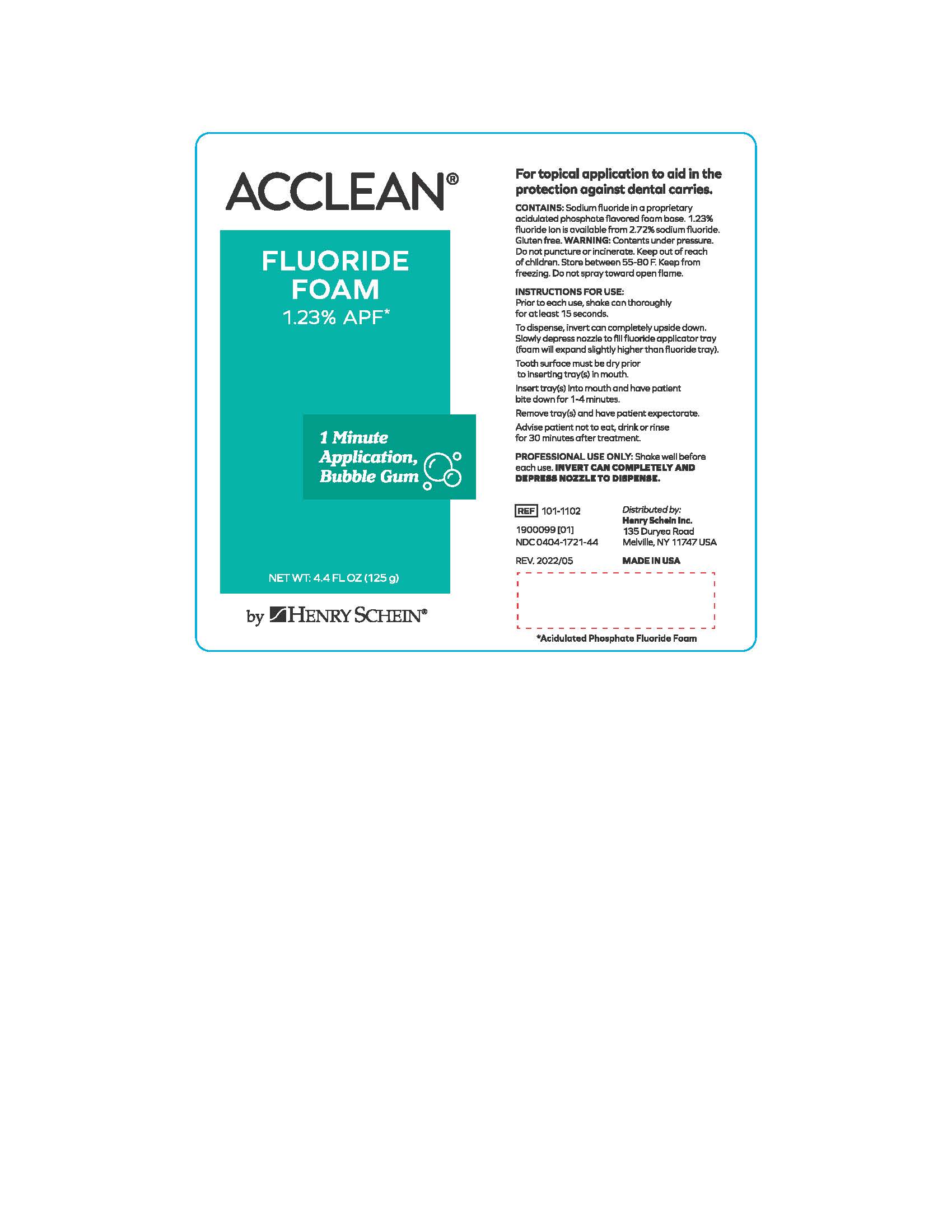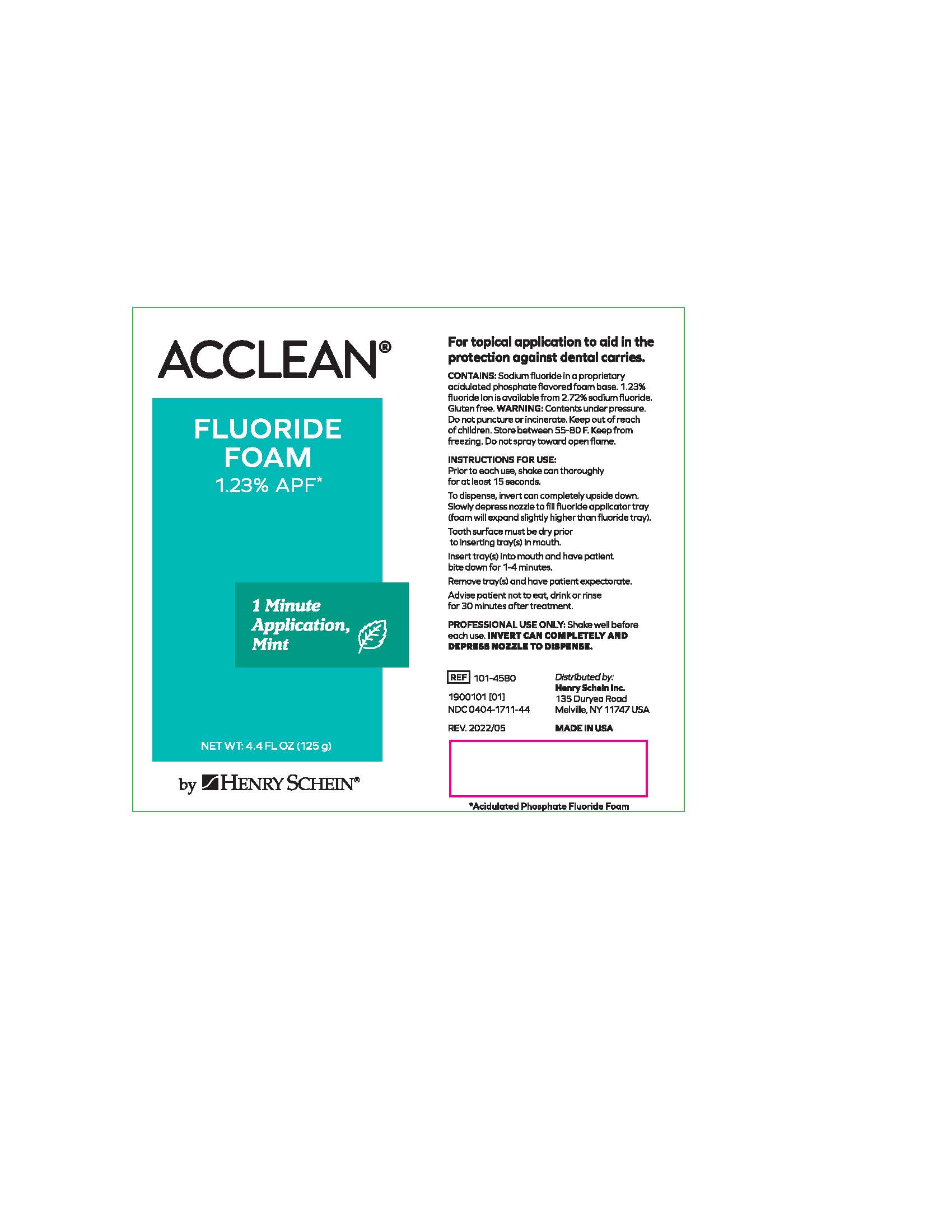 DRUG LABEL: Acclean Foam Fluoride 60 Second Application
NDC: 0404-1731 | Form: AEROSOL, FOAM
Manufacturer: Henry Schein
Category: prescription | Type: HUMAN PRESCRIPTION DRUG LABEL
Date: 20231003

ACTIVE INGREDIENTS: SODIUM FLUORIDE 0.0272 g/1 g
INACTIVE INGREDIENTS: SODIUM PHOSPHATE, MONOBASIC, ANHYDROUS; BETAINE; XYLITOL; POLOXAMER 407; SUCRALOSE

ACCLEAN
Foam Fluoride
60 Second Application

General Information

Henry Schein, Inc.

Acclean Foam Fluoride 60 Second Application

Acidulated Phosphate Fluoride Foam (1.23% Fluoride Ion)

Contains:

Sodium fluoride in a proprietary acidulated phophate flavored foam base. 1.23% fluoride ion is available from 2.72% sodium fluoride. Does not contain chlorofluorocarbon propellant.

Gluten free.

Indications

For topical application to aid in the protection against dental caries.

Warnings

Contens under pressure. Do not puncture or incinerate. Keep out of reach of children. Store between 50-80F. Keep from freezing. do not spray toward open flame.

Instructions For Use

- Prior to each use, shake can thoroughly for at least 15 seconds.
- To dispense, invert can completely upside down. Slowly depress nozzle to fill fluoride applicator tray (foam will expand slightly higher than fluoride tray).
- Tooth surface must be dry prior to inserting tray(s) in mouth.
- Insert tray(s) into mouth and have patient bite down for 1-4 minutes.
- Remove tray(s) and have patient expectorate.
- Advise patient not to eat, drink or rinse for 30 minutes after treatment.

Professional Use Only